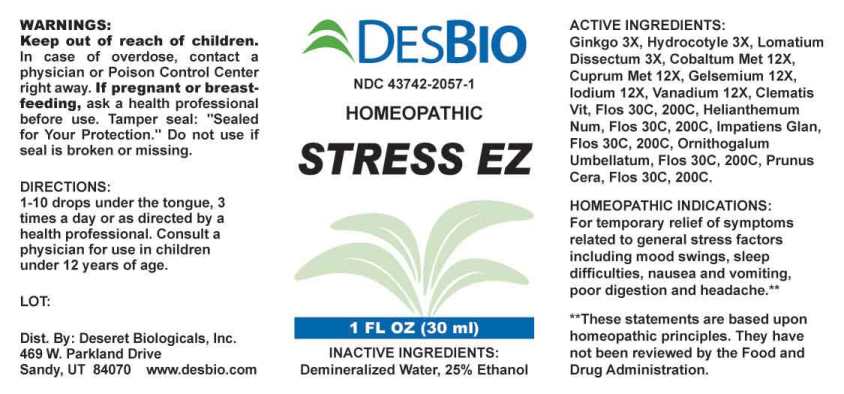 DRUG LABEL: Stress
NDC: 43742-2057 | Form: LIQUID
Manufacturer: Deseret Biologicals, Inc.
Category: homeopathic | Type: HUMAN OTC DRUG LABEL
Date: 20220728

ACTIVE INGREDIENTS: GINKGO 3 [hp_X]/1 mL; CENTELLA ASIATICA WHOLE 3 [hp_X]/1 mL; LOMATIUM DISSECTUM ROOT 3 [hp_X]/1 mL; COBALT 12 [hp_X]/1 mL; COPPER 12 [hp_X]/1 mL; GELSEMIUM SEMPERVIRENS ROOT 12 [hp_X]/1 mL; IODINE 12 [hp_X]/1 mL; VANADIUM 12 [hp_X]/1 mL; CLEMATIS VITALBA FLOWER 30 [hp_C]/1 mL; HELIANTHEMUM NUMMULARIUM FLOWER 30 [hp_C]/1 mL; IMPATIENS GLANDULIFERA FLOWER 30 [hp_C]/1 mL; ORNITHOGALUM UMBELLATUM FLOWERING TOP 30 [hp_C]/1 mL; PRUNUS CERASIFERA FLOWER 30 [hp_C]/1 mL
INACTIVE INGREDIENTS: WATER; ALCOHOL

DRUG FACTS:

ACTIVE INGREDIENTS:

Ginkgo Biloba 3X, Hydrocotyle Asiatica 3X, Lomatium Dissectum 3X, Cobaltum Metallicum 12X, Cuprum Metallicum 12X, Gelsemium Sempervirens 12X, Iodium 12X, Vanadium Metallicum 12X, Clematis Vitalba, Flos 30C, 200C, Helianthemum Nummularium, Flos 30C, 200C, Impatiens Glandulifera, Flos 30C, 200C, Ornithogalum Umbellatum, Flos 30C, 200C, Prunus Cerasifera, Flos 30C, 200C

HOMEOPATHIC INDICATIONS:

For temporary relief of symptoms related to general stress factors including mood swings, sleep difficulties, nausea and vomiting, poor digestion and headache.**

**These statements are based upon homeopathic principles. They have not been reviewed by the Food and Drug Administration.

WARNINGS:

Keep out of reach of children. In case of overdose, contact a physician or Poison Control Center right away.

If pregnant of breast-feeding, ask a health professional before use.

Tamper seal: "Sealed for Your Protection." Do not use if seal is broken or missing.

Keep out of reach of children. In case of overdose, contact a physician or Poison Control Center right away.

DIRECTIONS:

1-10 drops under the tongue, 3 times a day or as directed by a health professional. Consult a physician for use in children under 12 years of age.

HOMEOPATHIC INDICATIONS:

For temporary relief of symptoms related to general stress factors including mood swings, sleep difficulties, nausea and vomiting, poor digestion and headache.**

**These statements are based upon homeopathic principles. They have not been reviewed by the Food and Drug Administration.

INACTIVE INGREDIENTS:

Demineralized Water, 25% Ethanol

QUESTIONS:

Dist. By: Deseret Biologicals, Inc.

469 W. Parkland Drive

Sandy, UT 84070 www.desbio.com

PACKAGE LABEL DISPLAY:

DESBIO

NDC 43742-2057-1
HOMEOPATHIC

STRESS EZ

1 FL OZ (30 ml)